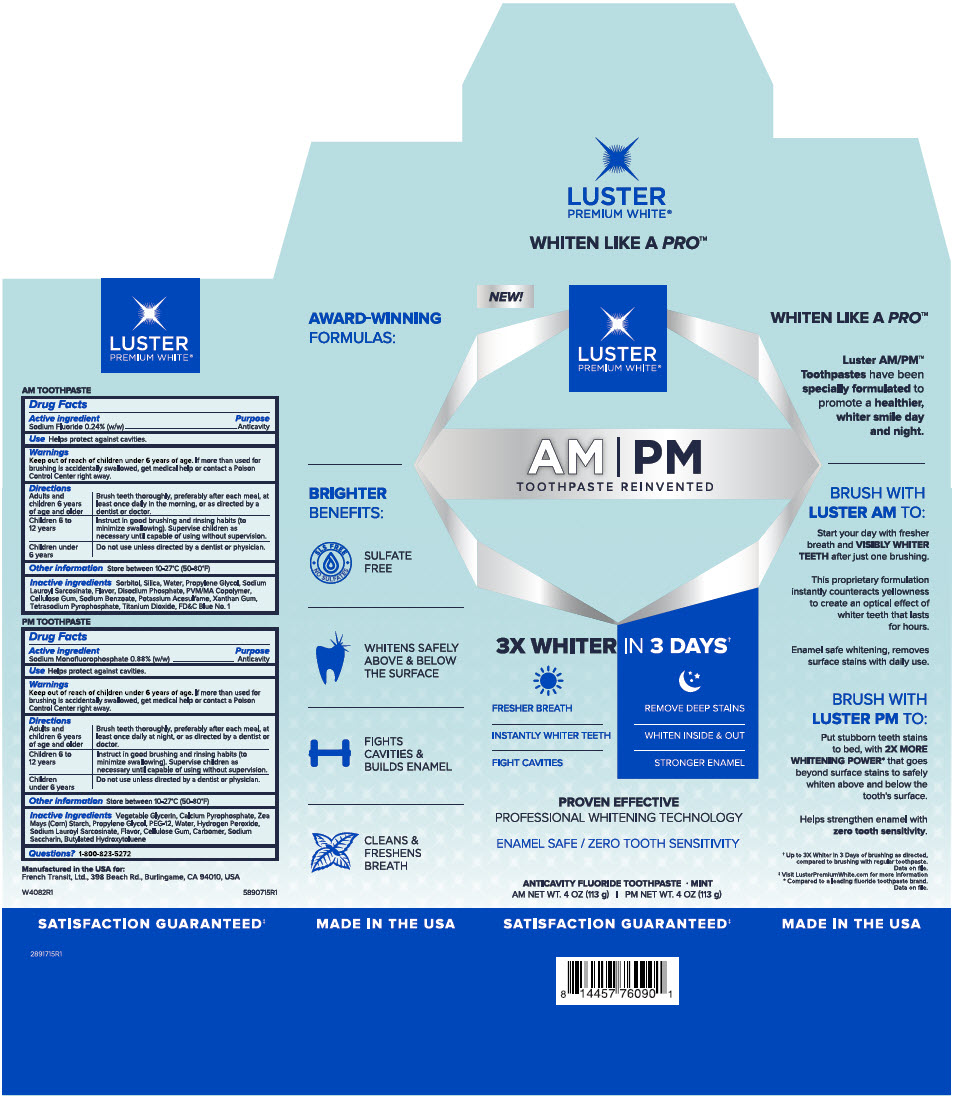 DRUG LABEL: Luster Premium White 
NDC: 72805-120 | Form: KIT | Route: DENTAL
Manufacturer: French Transit, Ltd.
Category: otc | Type: HUMAN OTC DRUG LABEL
Date: 20220112

ACTIVE INGREDIENTS: Sodium Fluoride 0.24 g/100 g; Sodium Monofluorophosphate 0.88 g/100 g
INACTIVE INGREDIENTS: Sorbitol; Silicon Dioxide; Water; Propylene Glycol; Sodium Lauroyl Sarcosinate; FD&C Blue No. 1; Sodium Phosphate, Dibasic, Anhydrous; Carboxymethylcellulose Sodium, unspecified; Sodium Benzoate; Acesulfame Potassium; Titanium Dioxide; Xanthan Gum; Sodium Pyrophosphate; Water; Calcium Pyrophosphate; Starch, Corn; Propylene Glycol; Polyethylene Glycol 600; Hydrogen Peroxide; Sodium Lauroyl Sarcosinate; Carboxymethylcellulose Sodium, unspecified; Carbomer Homopolymer Type A (Allyl Pentaerythritol Crosslinked); Saccharin Sodium; Butylated Hydroxytoluene

Luster Premium White®
AM/PM

AM TOOTHPASTE

Drug Facts

Active ingredient

Sodium Fluoride 0.24% (w/w)

Purpose

Anticavity

Use

Helps protect against cavities.

Warnings

Keep out of reach of children under 6 years of age. If more than used for brushing is accidentally swallowed, get medical help or contact a Poison Control Center right away.

Directions

Adults and children 6 years of age and older | Brush teeth thoroughly, preferably after each meal, at least once daily in the morning, or as directed by a dentist or doctor.
Children 6 to 12 years | Instruct in good brushing and rinsing habits (to minimize swallowing). Supervise children as necessary until capable of using without supervision.
Children under 6 years | Do not use unless directed by a dentist or physician.

Other information

Store between 10-27°C (50-80°F)

Inactive ingredients

Sorbitol, Silica, Water, Propylene Glycol, Sodium Lauroyl Sarcosinate, Flavor, Disodium Phosphate, PVM/MA Copolymer, Cellulose Gum, Sodium Benzoate, Potassium Acesulfame, Xanthan Gum, Tetrasodium Pyrophosphate, Titanium Dioxide, FD&C Blue No. 1

PM TOOTHPASTE

Drug Facts

Active ingredient

Sodium Monofluorophosphate 0.88% (w/w)

Purpose

Anticavity

Use

Helps protect against cavities.

Warnings

Keep out of reach of children under 6 years of age. If more than used for brushing is accidentally swallowed, get medical help or contact a Poison Control Center right away.

Directions

Adults and children 6 years of age and older | Brush teeth thoroughly, preferably after each meal, at least once daily at night, or as directed by a dentist or doctor.
Children 6 to 12 years | Instruct in good brushing and rinsing habits (to minimize swallowing). Supervise children as necessary until capable of using without supervision.
Children under 6 years | Do not use unless directed by a dentist or physician.

Other information

Store between 10-27°C (50-80°F)

Inactive Ingredients

Vegetable Glycerin, Calcium Pyrophosphate, Zea Mays (Corn) Starch, Propylene Glycol, PEG-12, Water, Hydrogen Peroxide, Sodium Lauroyl Sarcosinate, Flavor, Cellulose Gum, Carbomer, Sodium Saccharin, Butylated Hydroxytoluene

Questions?

1-800-823-5272

PRINCIPAL DISPLAY PANEL - Kit Carton

NEW!

LUSTER
PREMIUM WHITE®

AM | PM
TOOTHPASTE REINVENTED

3X WHITER IN 3 DAYS†

FRESHER BREATH

INSTANTLY WHITER TEETH

FIGHT CAVITIES

REMOVE DEEP STAINS

WHITEN INSIDE & OUT

STRONGER ENAMEL

PROVEN EFFECTIVE
PROFESSIONAL WHITENING TECHNOLOGY

ENAMEL SAFE / ZERO TOOTH SENSITIVITY

ANTICAVITY FLUORIDE TOOTHPASTE • MINT
AM NET WT. 4 OZ (113 g) | PM NET WT. 4 OZ (113 g)

SATISFACTION GUARANTEED‡